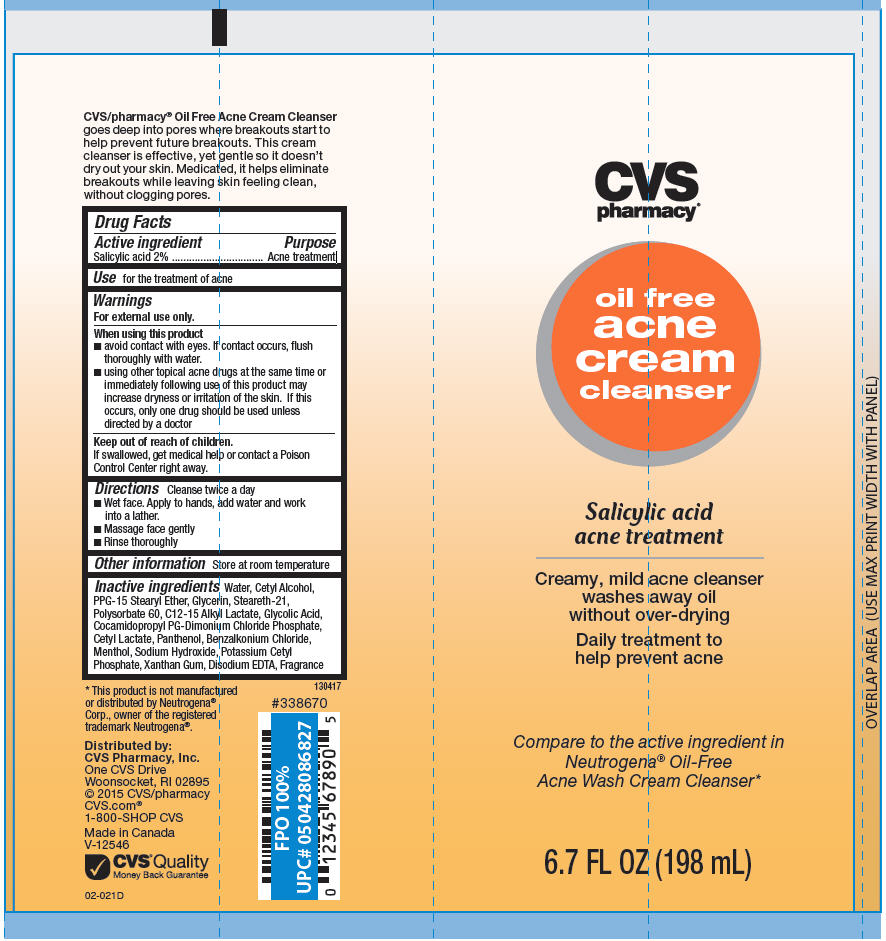 DRUG LABEL: CVS Oil Free Acne Cleanser 
NDC: 69842-580 | Form: CREAM
Manufacturer: CVS Health
Category: otc | Type: HUMAN OTC DRUG LABEL
Date: 20220124

ACTIVE INGREDIENTS: Salicylic Acid 20 mg/1 mL
INACTIVE INGREDIENTS: Water; Cetyl Alcohol; PPG-15 Stearyl Ether; Glycerin; Steareth-21; Polysorbate 60; C12-15 Alkyl Lactate; Glycolic Acid; Cocamidopropyl Propylene Glycol-Dimonium Chloride Phosphate; Cetyl Lactate; Panthenol; Benzalkonium Chloride; Menthol, Unspecified Form; Sodium Hydroxide; Potassium Cetyl Phosphate; Xanthan Gum; Edetate Disodium

CVS Oil Free Acne Cream Cleanser
Acne Treatment

Drug Facts

Active ingredient

Salicylic acid 2%

Purpose

Acne treatment

Use

for the treatment of acne

Warnings

For external use only.

When using this product

- avoid contact with eyes. If contact occurs, flush thoroughly with water.
- using other topical acne drugs at the same time or immediately following use of this product may increase dryness or irritation of the skin. If this occurs, only one drug should be used unless directed by a doctor

Keep out of reach of children.

If swallowed, get medical help or contact a Poison Control Center right away.

Directions

Cleanse twice a day

- Wet face. Apply to hands, add water and work into a lather.
- Massage face gently
- Rinse thoroughly

Other information

Store at room temperature

Inactive ingredients

Water, Cetyl Alcohol, PPG-15 Stearyl Ether, Glycerin, Steareth-21, Polysorbate 60, C12-15 Alkyl Lactate, Glycolic Acid, Cocamidopropyl PG-Dimonium Chloride Phosphate, Cetyl Lactate, Panthenol, Benzalkonium Chloride, Menthol, Sodium Hydroxide, Potassium Cetyl Phosphate, Xanthan Gum, Disodium EDTA, Fragrance

Distributed by:
CVS Pharmacy, Inc.
One CVS Drive
Woonsocket, RI 02895

PRINCIPAL DISPLAY PANEL - 198 mL Tube Label

CVS
pharmacy®

oil free
acne
cream
cleanser

Salicylic acid
acne treatment

Creamy, mild acne cleanser
washes away oil
without over-drying

Daily treatment to
help prevent acne

Compare to the active ingredient in
Neutrogena® Oil-Free
Acne Wash Cream Cleanser*

6.7 FL OZ (198 mL)